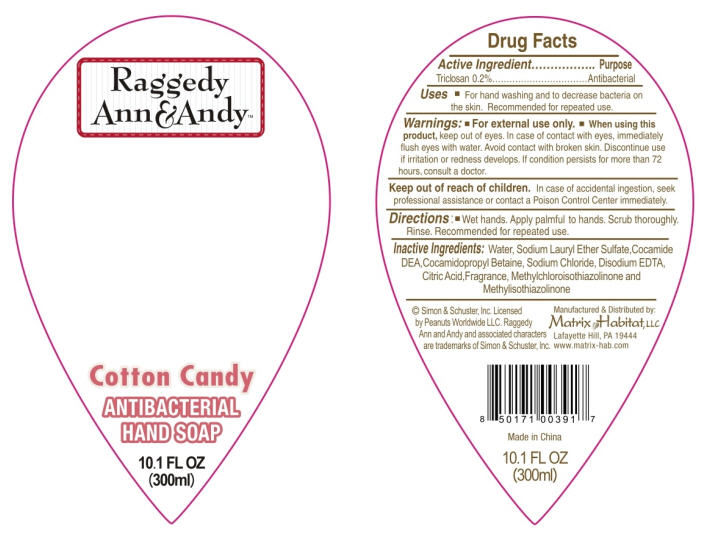 DRUG LABEL: Raggedy Ann and Andy 
NDC: 75878-001 | Form: SOAP
Manufacturer: My Habitat Brands LLC
Category: otc | Type: HUMAN OTC DRUG LABEL
Date: 20101206

ACTIVE INGREDIENTS: Triclosan 0.002 g/1 mL
INACTIVE INGREDIENTS: Water; sodium lauryl sulfate; Coco Diethanolamide; Cocamidopropyl Betaine; sodium chloride; edetate disodium; citric acid monohydrate; methylchloroisothiazolinone; methylisothiazolinone

Raggedy
Ann&Andy™
Cotton Candy
ANTIBACTERIAL
HAND SOAP

Active Ingredient

Triclosan 0.2%

Purpose

Antibacterial

Uses

- For hand washing and to decrease bacteria on the skin. Recommended for repeated use.

Warnings

- For external use only.

- When using this product, keep out of eyes. In case of contact with eyes, immediately flush eyes with water. Avoid contact with broken skin. Discontinue use if irritation of redness develops. If condition persists for more than 72 hours, consult a doctor.

Keep out of reach of children. In case of accidental ingestion, seek professional assistance or contact a Poison Control Center immediately.

Directions

- Wet hands. Apply palmful to hands. Scrub thoroughly. Rinse. Recommended for repeated use.

Inactive Ingredients

Water, Sodium Lauryl Ether Sulfate,Cocamide DEA,Cocamidopropyl Betaine, Sodium Chloride, Disodium EDTA, Citric Acid,Fragrance, Methylchloroisothiazolinone and Methylisothiazolinone

PRINCIPAL DISPLAY PANEL - 300ml Bottle Label

Raggedy
Ann&Andy™

Cotton Candy

ANTIBACTERIAL
HAND SOAP

10.1 FL OZ
(300ml)